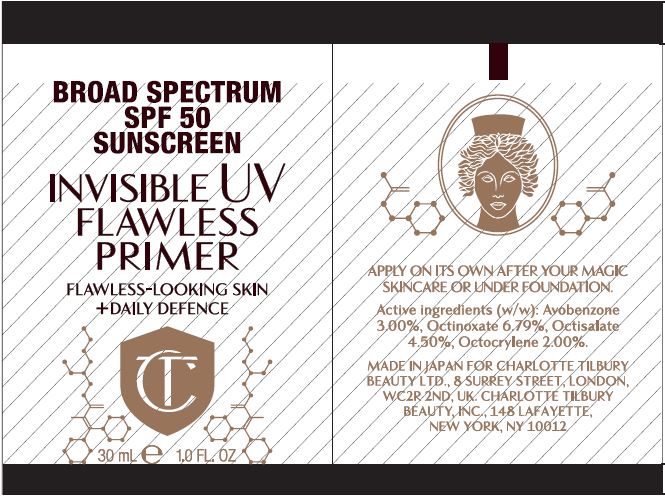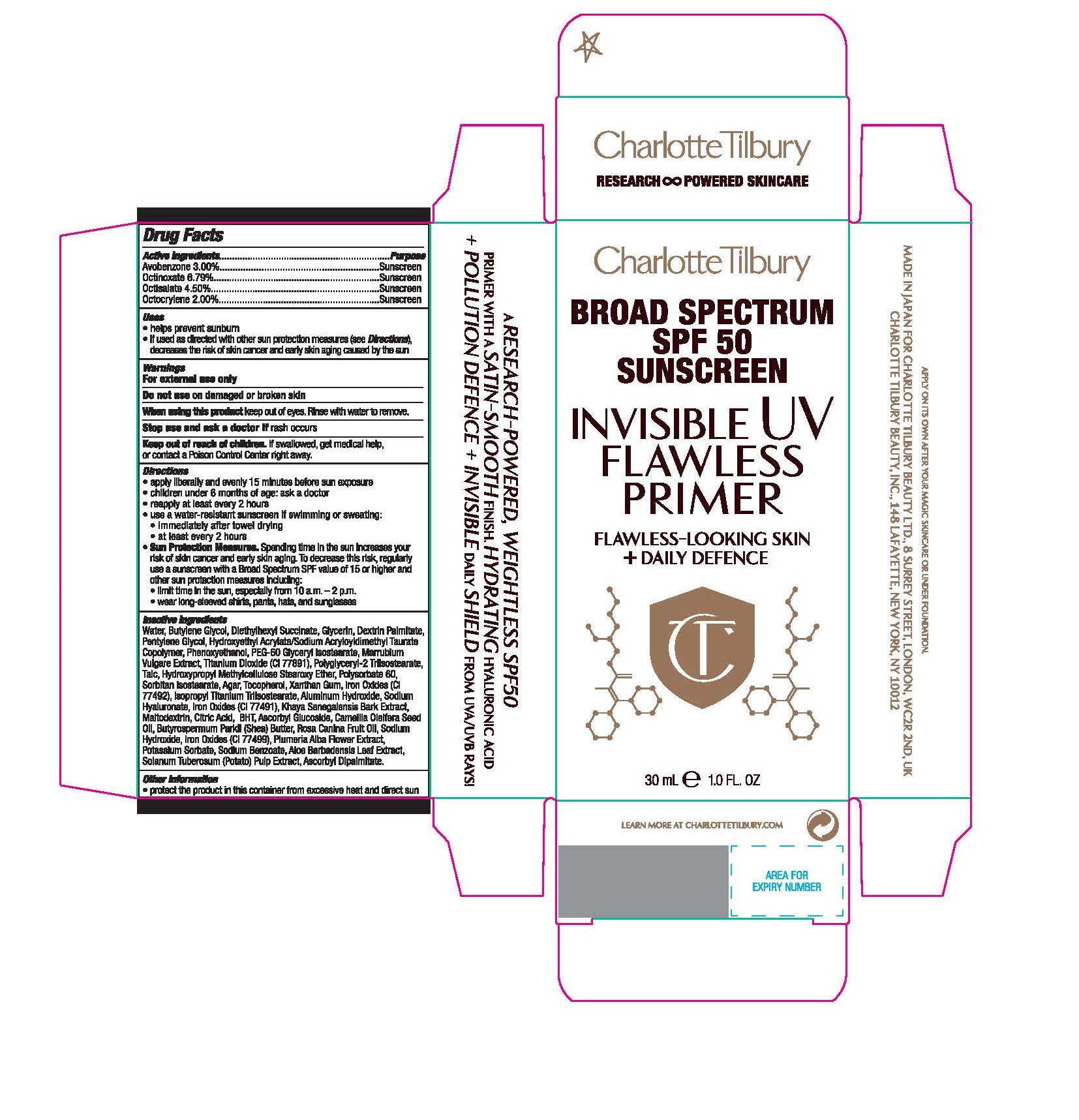 DRUG LABEL: CHARLOTTE TILBURY Broad Spectrum SPF 50 Sunscreen Invisible UV Flawless Primer
NDC: 70186-700 | Form: CREAM
Manufacturer: Charlotte Tilbury Beauty Ltd.
Category: otc | Type: HUMAN OTC DRUG LABEL
Date: 20220715

ACTIVE INGREDIENTS: OCTINOXATE 2.038 g/30 mL; AVOBENZONE 0.918 g/30 mL; OCTISALATE 1.377 g/30 mL; OCTOCRYLENE 0.612 g/30 mL
INACTIVE INGREDIENTS: DEXTRIN PALMITATE (CORN; 20000 MW); PHENOXYETHANOL; PEG-60 GLYCERYL ISOSTEARATE; POLYSORBATE 60; SORBITAN ISOSTEARATE; TOCOPHEROL; XANTHAN GUM; TALC; GLYCERIN; BUTYLENE GLYCOL; DIETHYLHEXYL SUCCINATE; AGAR; ALUMINUM HYDROXIDE; BUTYLATED HYDROXYTOLUENE; SODIUM HYDROXIDE; FERROSOFERRIC OXIDE; HYPROMELLOSE 2910 0.45% STEAROXY ETHER; MALTODEXTRIN; ROSA CANINA FRUIT OIL; FERRIC OXIDE YELLOW; HYALURONATE SODIUM; FERRIC OXIDE RED; SODIUM BENZOATE; ASCORBYL GLUCOSIDE; ASCORBYL DIPALMITATE; HOREHOUND; TITANIUM DIOXIDE; POLYGLYCERYL-2 TRIISOSTEARATE; PLUMERIA ALBA FLOWER; POTASSIUM SORBATE; ALOE VERA LEAF; POTATO PULP; PENTYLENE GLYCOL; HYDROXYETHYL ACRYLATE/SODIUM ACRYLOYLDIMETHYL TAURATE COPOLYMER (45000 MPA.S AT 1%); WATER; CAMELLIA OIL; SHEA BUTTER; ISOPROPYL TITANIUM TRIISOSTEARATE; KHAYA SENEGALENSIS BARK; ANHYDROUS CITRIC ACID

CHARLOTTE TILBURY Broad Spectrum SPF 50 Sunscreen Invisible UV Flawless Primer

DRUG FACTS Active ingredients

Avobenzone 3.00%

Octinoxate 6.79%

Octisalate 4.50%

Octocrylene 2.00%

Purpose

Sunscreen

Uses

- helps prevent sunburn

- if used as directed with other sun protection measures (see Directions), decreases the risk of skin cancer and early skin aging caused by the sun

Warnings

For external use only

Do not use on damaged or broken skin

When using this product keep out of eyes. Rinse with water to remove.

Stop use and ask a doctor if rash occurs.

Keep out of reach of children. If swallowed, get medical help, or contact a Poison Control Center right away.

Directions

- apply liberally and evenly 15 minutes before sun exposure
- children under 6 months of age: ask a doctor
- reapply at least every 2 hours
- use a water-resistant sunscreen if swimming or sweating:

- immediately after towel drying

- at least every 2 hours

- Sun Protection Measures. Spending time in the sun increases your risk of skin cancer and early skin aging. To decrease this risk, regularly use a sunscreen with a Broad Spectrum SPF value of 15 or higher and other sun protection measures including:

- limit time in the sun, especially from 10 am - 2pm

- wear long-sleeved shirts, pants, hats, and sunglasses

Inactive ingredients

Water, Butylene Glycol, Diethylhexyl Succinate, Glycerin, Dextrin Palmitate, Pentylene Glycol, Hydroxyethyl Acrylate/Sodium Acryloyldimethyl Taurate Copolymer, Phenoxyethanol, PEG-60 Glyceryl Isostearate, Marrubium Vulgare Extract, Titanium Dioxide (CI 77891), Polyglyceryl-2 Triisostearate, Talc, Hydroxypropyl Methylcellulose Stearoxy Ether, Polysorbate 60, Sorbitan Isostearate, Agar, Tocopherol, Xanthan Gum, Iron Oxides (CI 77492), Isopropyl Titanium Triisostearate, Aluminum Hydroxide, Sodium Hyaluronate, Iron Oxides (CI 77491), Khaya Senegalensis Bark Extract, Maltodextrin, Citric Acid, BHT, Ascorbyl Glucoside, Camellia Oleifera Seed Oil, Butyrospermum Parkii (Shea) Butter, Rosa Canina Fruit Oil, Sodium Hydroxide, Iron Oxides (CI 77499), Plumeria Alba Flower Extract, Potassium Sorbate, Sodium Benzoate, Aloe Barbadensis Leaf Extract, Solanum Tuberosum (Potato) Pulp Extract, Ascorbyl Dipalmitate.

Other information

Protect the product in this container from excessive heat and direct sun

PACKAGE LABEL

Charlotte Tilbury

BROAD SPECTRUM

SPF 50

SUNSCREEN

INVISIBLE UV

FLAWLESS

PRIMER

30 mL